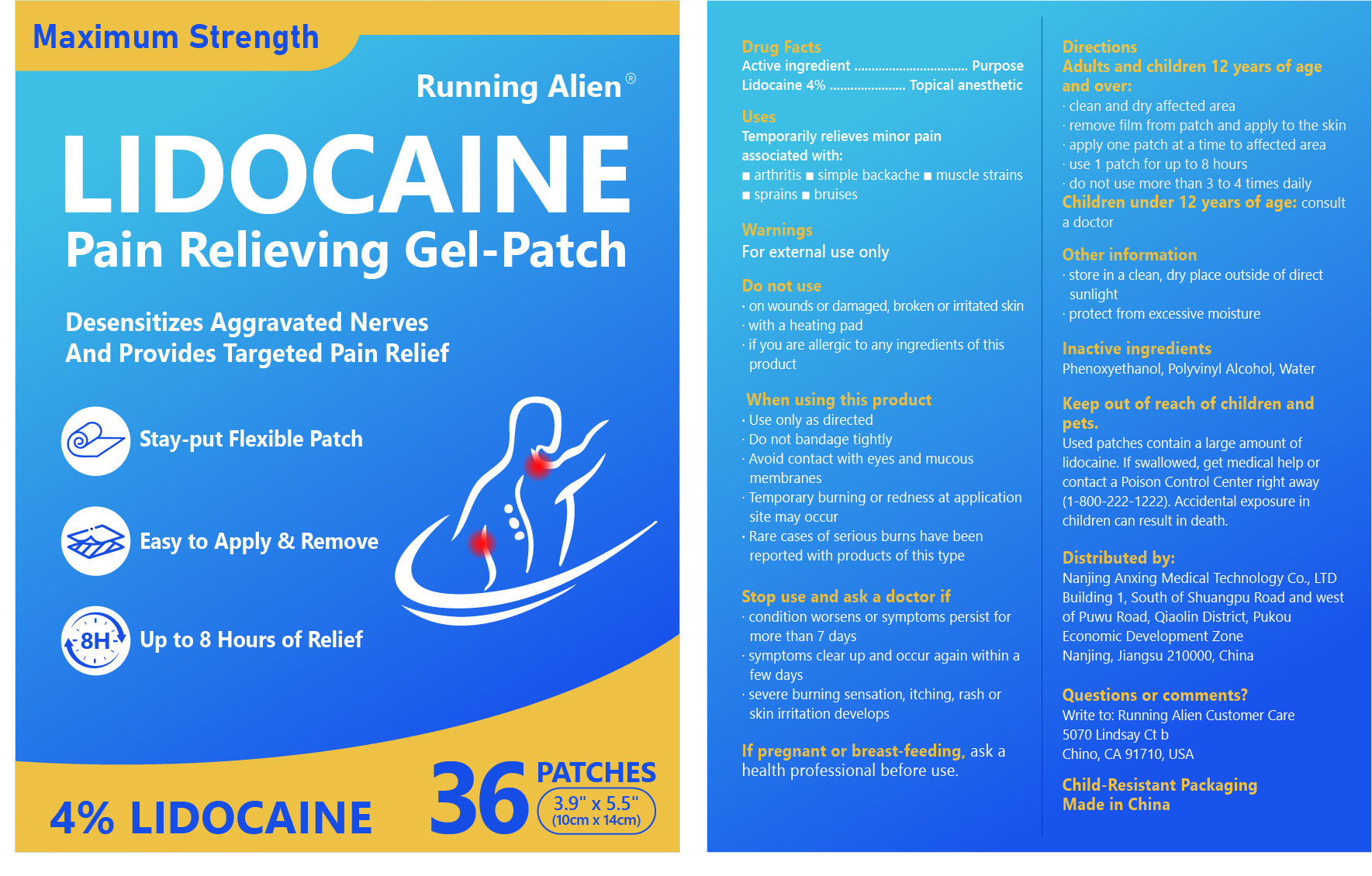 DRUG LABEL: Lidocaine Pain Relieving Gel-Patch
NDC: 87125-001 | Form: PATCH
Manufacturer: Nanjing Anxing Medical Technology Co., Ltd.
Category: otc | Type: HUMAN OTC DRUG LABEL
Date: 20251010

ACTIVE INGREDIENTS: LIDOCAINE HYDROCHLORIDE ANHYDROUS 0.04 g/1 1
INACTIVE INGREDIENTS: WATER; PHENOXYETHANOL; POLYVINYL ALCOHOL

87125-001 Lidocaine Pain Relieving Gel-Patch

ACTIVE INGREDIENT

Lidocaine 4%

PURPOSE

Topical anesthetic

INDICATIONS AND USAGE

Temporarily relieves minor pain
associated with:
arthritis
simple backache
muscle strains
sprains
bruises

WARNINGS

For external use only

DO NOT USE

on wounds or damaged, broken or irritated skin
with a heating pad
if you are allergic to any ingredients of this product

WHEN USING

Use only as directed
Do not bandage tightly
Avoid contact with eyes and mucous membranes
Temporary burning or redness at application site may occur
Rare cases of serlous burns have been reported with products of this type

STOP USE

condition worsens or symptoms persist for more than 7 days
symptoms clear up and occur again within a few days
severe burning sensation, itching, rash or skin irritation develops
If pregnant or breast-feeding, ask a health professional before use.

KEEP OUT OF REACH OF CHILDREN

Used patches contain a large amount of lidocaine. lf swallowed, get medical help or contact a Poison Control Center right away (1-800-222-1222).Accidental exposure in children can result in death.

DOSAGE AND ADMINISTRATION

Adults and children 12 years of age and over:
clean and dry affected area
remove film from patch and apply to the skin
apply one patch at a time to affected area
use 1 patch for up to 8 hours
do not use more than 3 to 4 times daily
Children under 12 years of age: consult
a doctor

INACTIVE INGREDIENT

WATER
POLYVINYL ALCOHOL
PHENOXYETHANOL